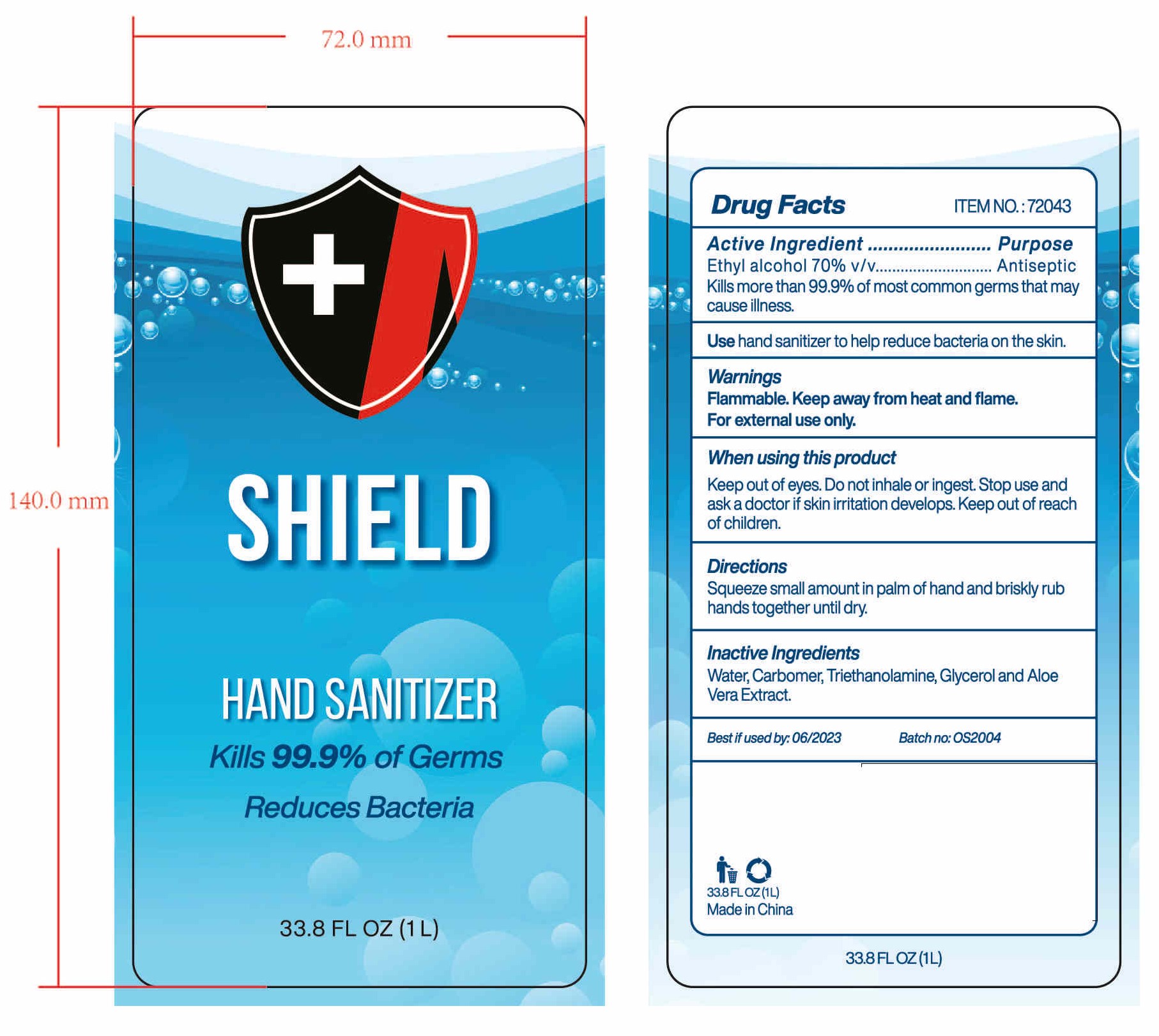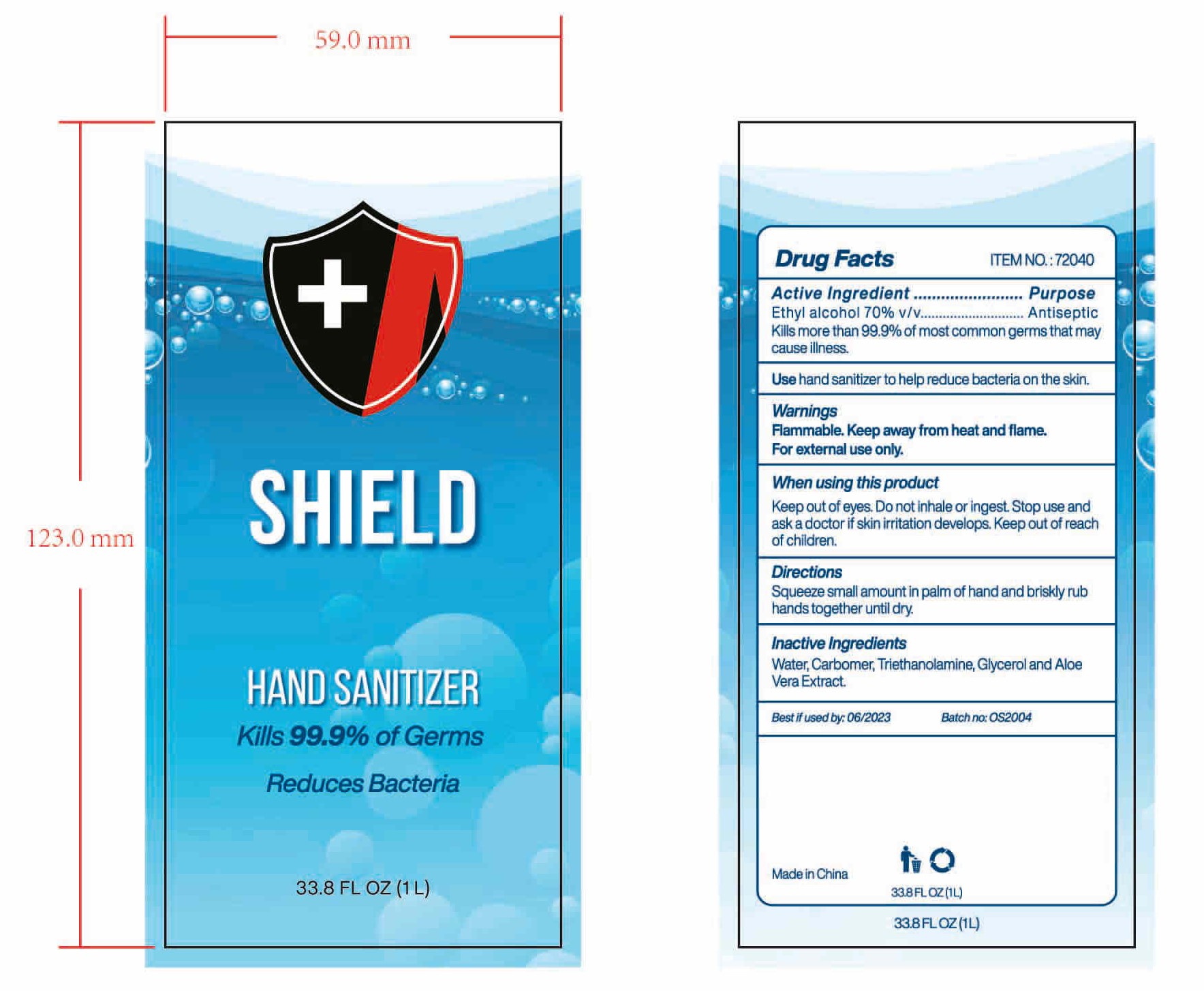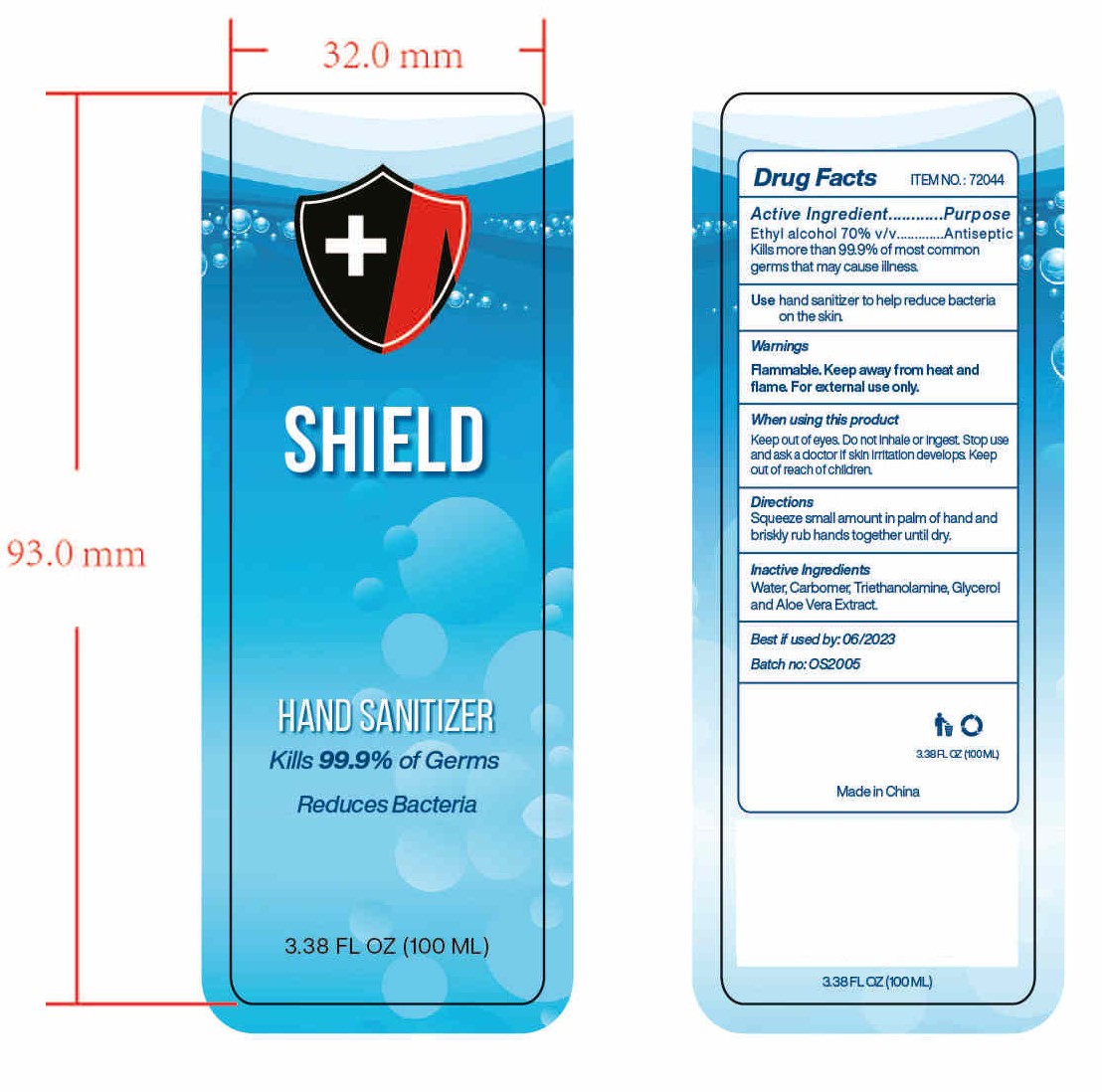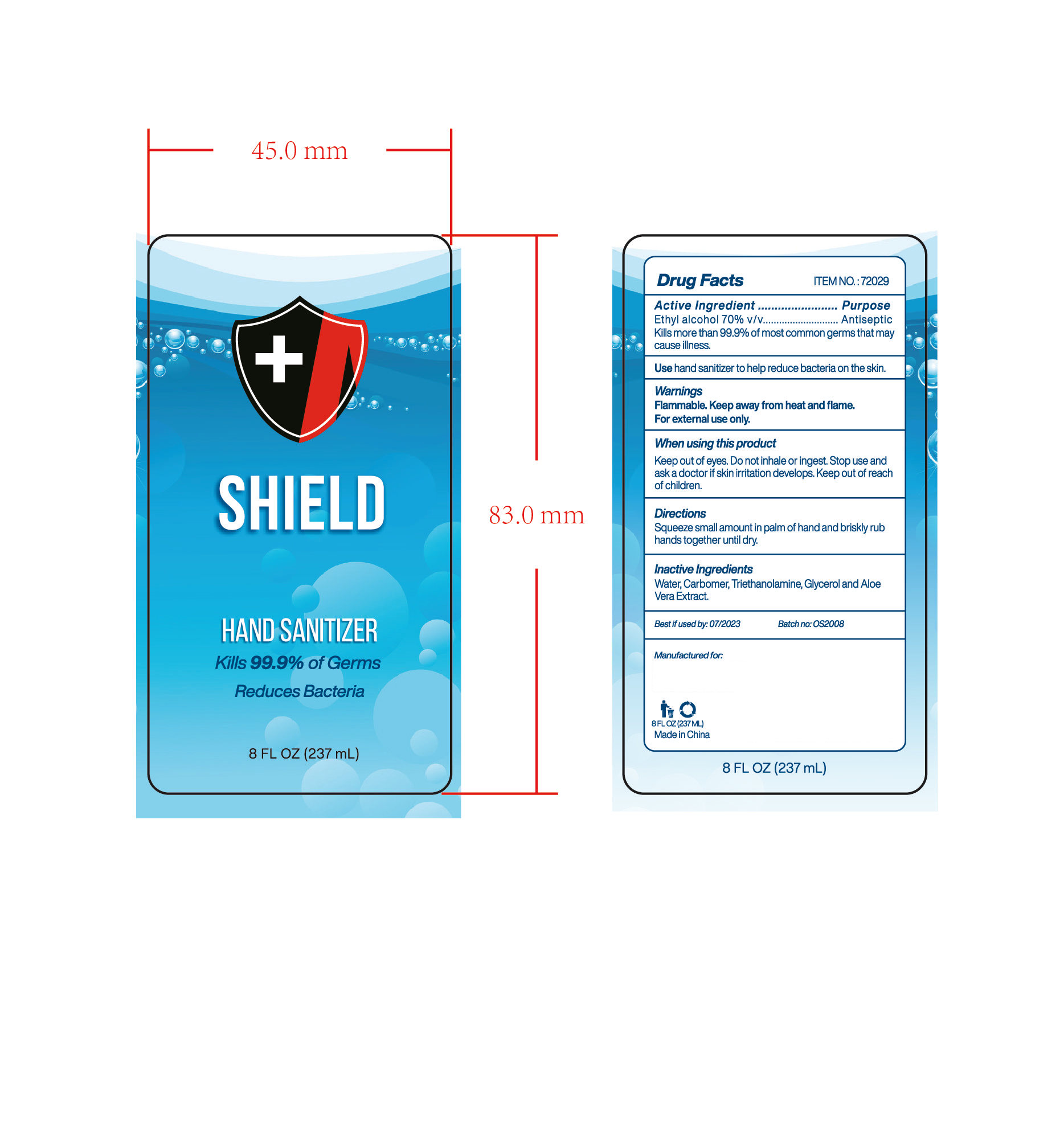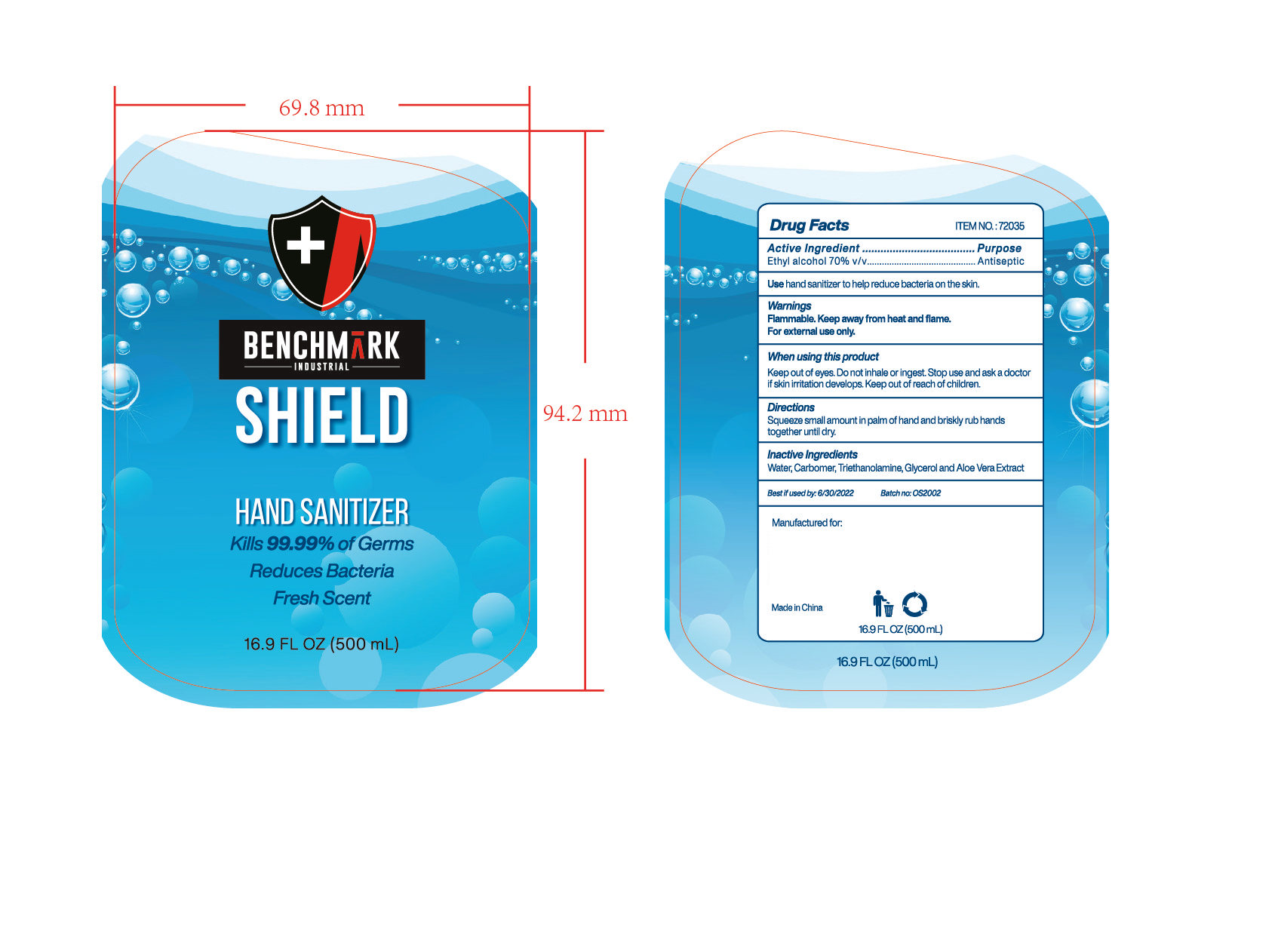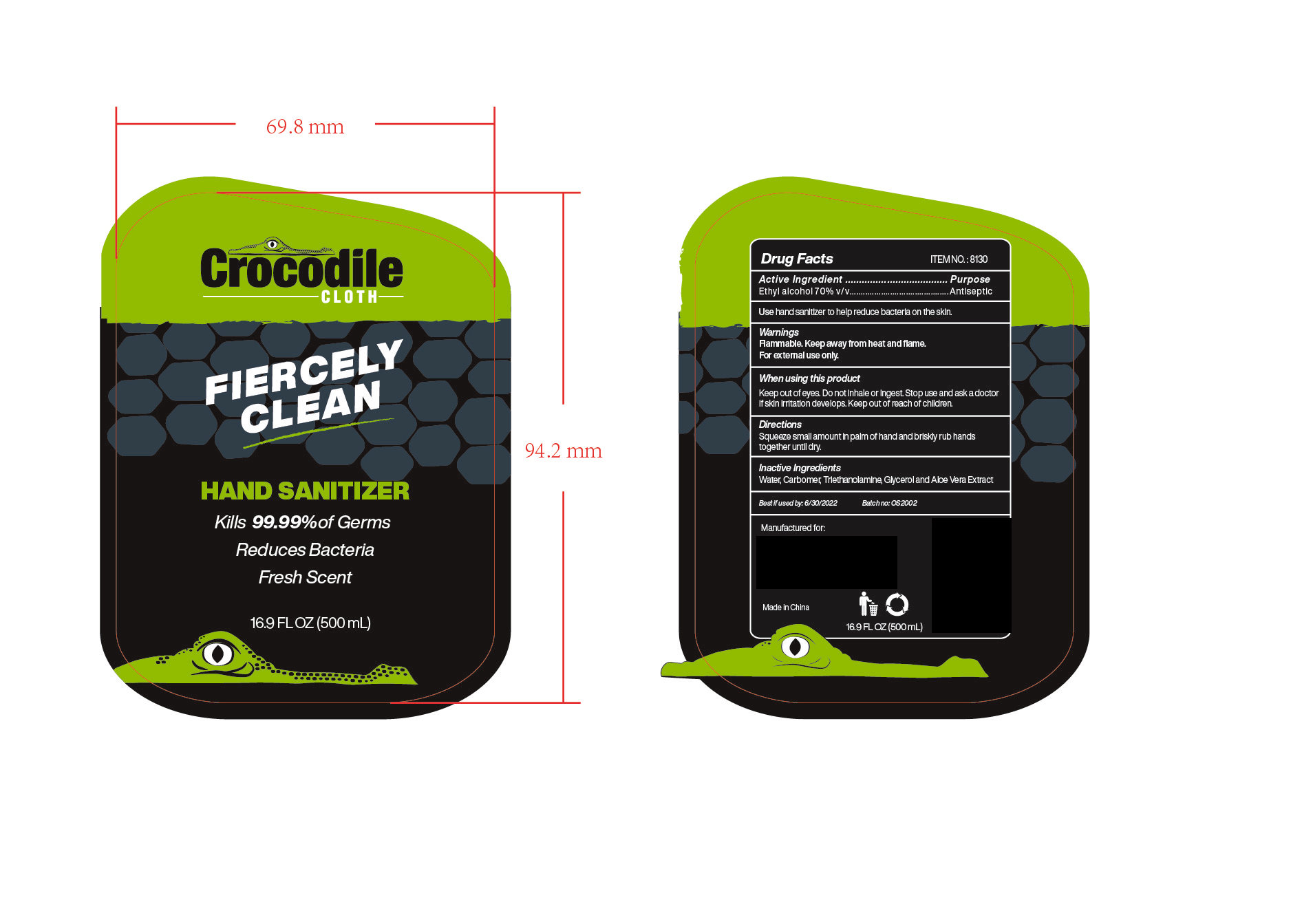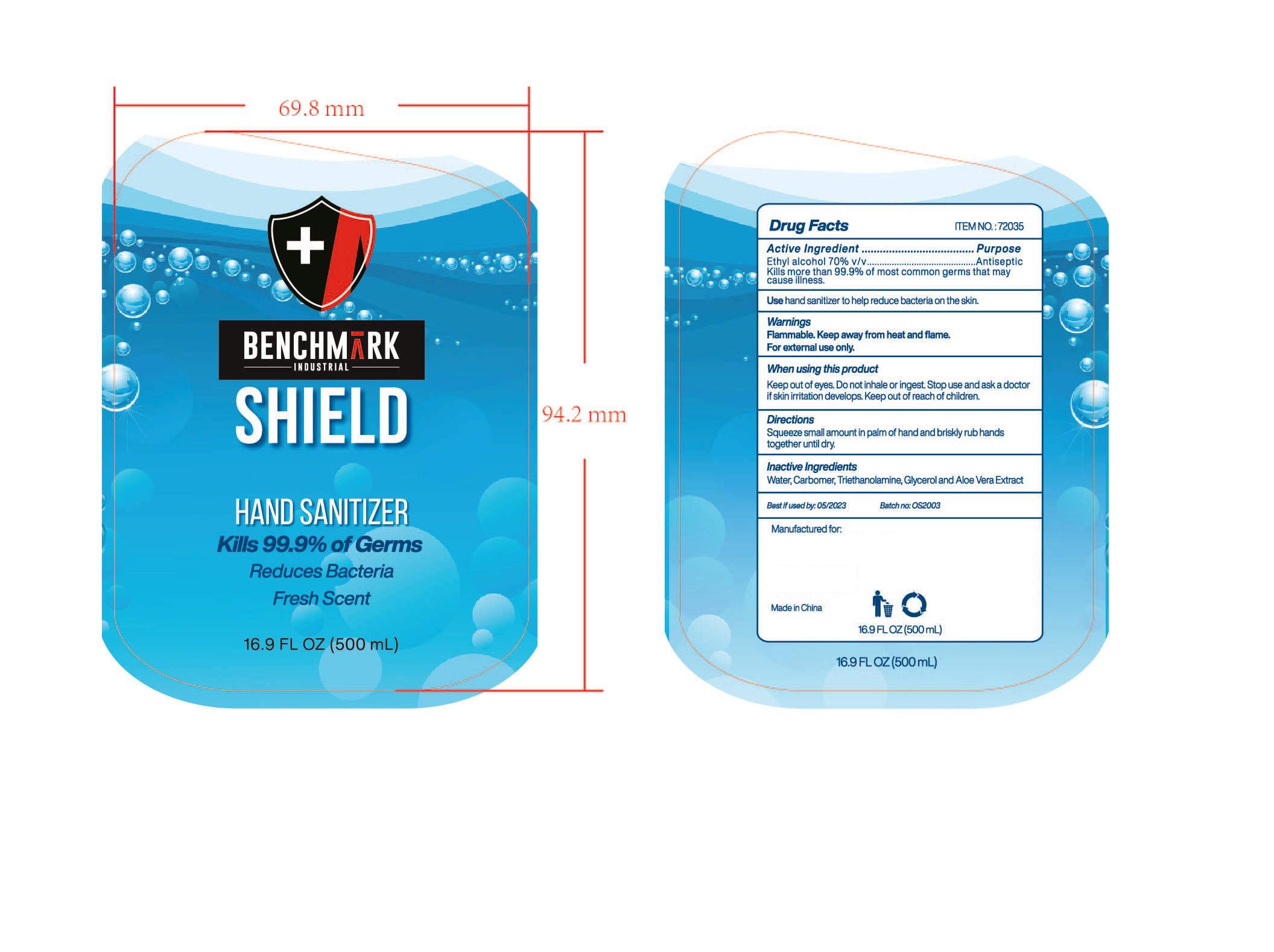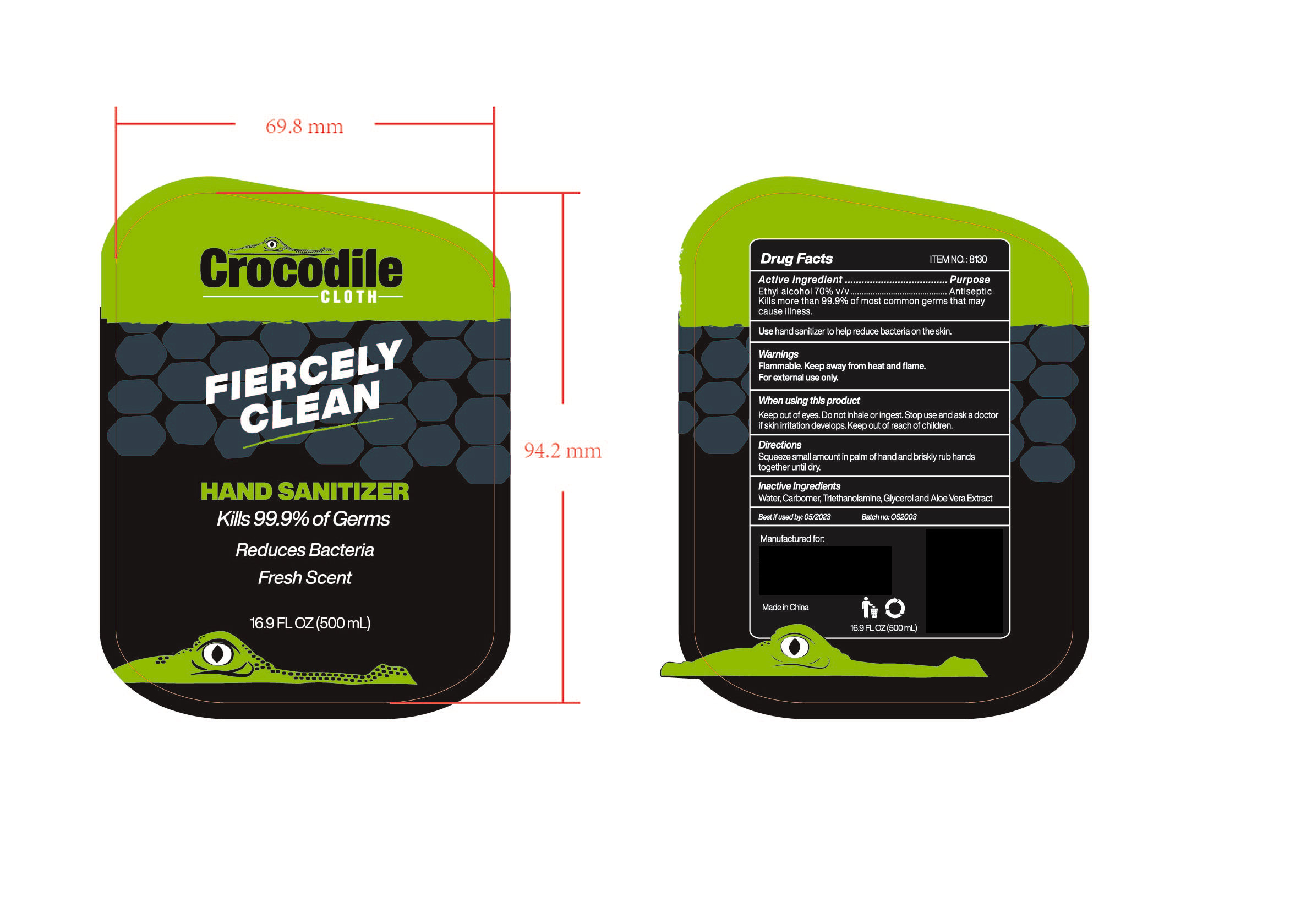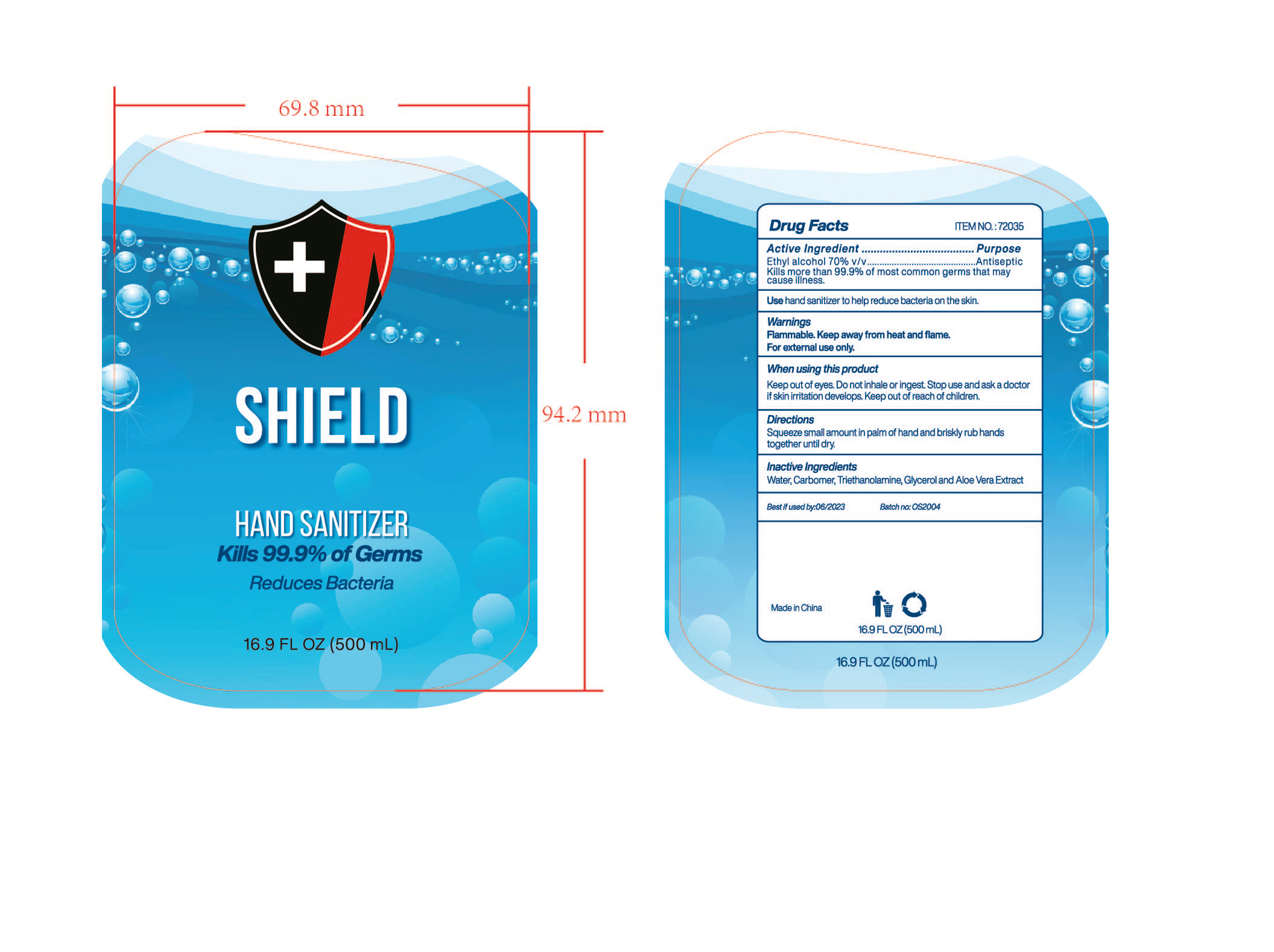 DRUG LABEL: HAND SANITIZER
NDC: 47993-260 | Form: GEL
Manufacturer: NINGBO JIANGBEI OCEAN STAR TRADING CO.,LTD
Category: otc | Type: HUMAN OTC DRUG LABEL
Date: 20201104

ACTIVE INGREDIENTS: ALCOHOL 70 mL/100 mL
INACTIVE INGREDIENTS: WATER; CARBOMER 940; TRIETHANOLAMINE BENZOATE; ALOE VERA LEAF; GLYCERIN

47993-260

Active ingredients

Ethyl Alcohol 70% v/v

PURPOSE

Antiseptic

Kill more than 99.9% of most common germs that my cause illness.

Uses：

Hand sanitizer to help reduce bacteria on the skin.

Warnings:

Flammable. keep away from heat and flame. For external use only.

When using this product.

Keep out of eyes. Do not inhale or ingest. Stop use and ask a doctor if skin irritation develops. Keep out of reach of children.

Keep out of reach of children.

Directions:

Squeeze small amount in palm of hand and briskly rub hands together until dry.

Inactive Ingredients:

Water,Carbomer,Triethanolamine,Glycerol and Aloe Vera Extract.